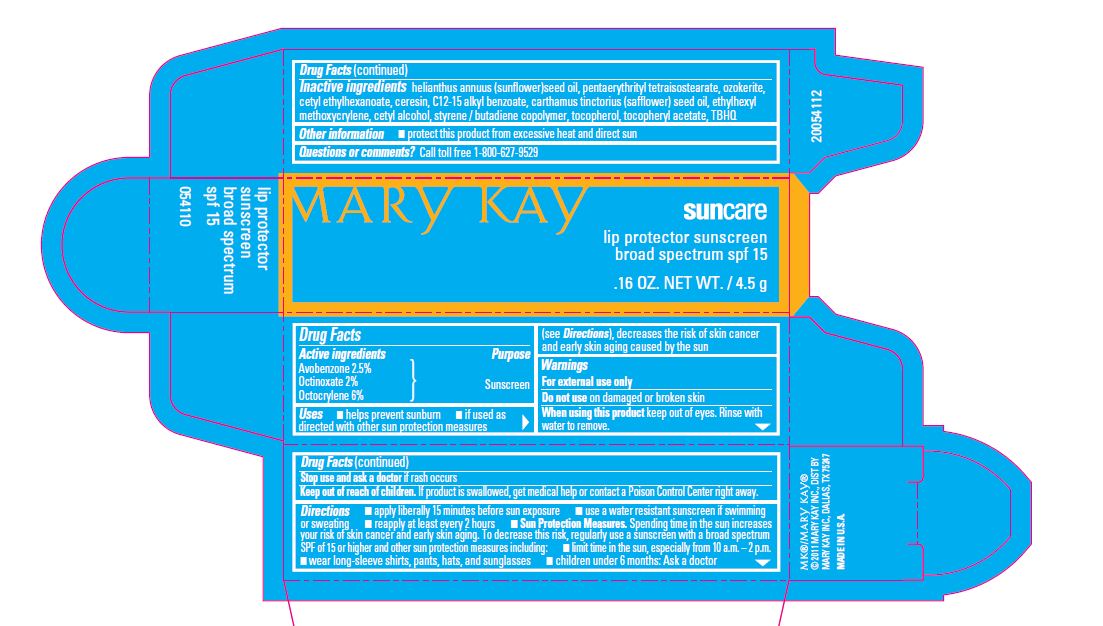 DRUG LABEL: New Lip Protector Sunscreen SPF15 
NDC: 51531-9500 | Form: LIPSTICK
Manufacturer: Mary Kay INC.
Category: otc | Type: HUMAN OTC DRUG LABEL
Date: 20120301

ACTIVE INGREDIENTS: Octinoxate 0.09 g/4.5 g; Avobenzone 0.1125 g/4.5 g; Octocrylene 0.27 g/4.5 g
INACTIVE INGREDIENTS: SUNFLOWER OIL; CERESIN; CETYL ALCOHOL ; CETYL ETHYLHEXANOATE; ALKYL (C12-15) BENZOATE; ALPHA-TOCOPHEROL; SAFFLOWER  OIL; ALPHA-TOCOPHEROL ACETATE

New Lip Protector Sunscreen SPF15

ACTIVE INGREDIENT

ACTIVE INGREDIENTS: AVOBENZONE 2.5% OCTINOXATE 2.0% OCTOCRYLENE 6.0%

INDICATIONS AND USAGE

DIRECTION: Apply liberally at least 15 minutes before sun exposure, use a water resistant sunscreen if swimming or sweating, reapply at least every 2hours.

Sun Protection Measures. Spending time in the sun increases your risk of skin cancer and early skin aging. To decrease the risk,regulary use a sunscreen with a broad spectrum SPF of 15 or

higher and other sun protection measures including. Limit time in sun, especially from 10 a.m. - 2 p.m. wear long - sleeve shirts pants,hats,and sunglasses.

WARNINGS

WARNING : For external use only. Do not use on damage or broken skin. When using this product keep out of eyes. Rinse with water to remove.

INACTIVE INGREDIENT

HELIANTHUS ANNUUS(SUNFLOWER)SEED OIL, PENTAETYTHRITYL TETRAISOSTEARATE , OZOKERITE, CETYL ETHYLHEXANOATE , CERESIN , C12-15 ALKYL BENZOATE , CARTHAMUS TINTORIUS (SAFFLOWER) SEED OIL , ETHYLHEXYL METHOXYCRYLENE, CETYL ALCOHOL , STYRENE / BUTADIENE COPOLYMER , TOCOPEROL ,TOCOPHERYL ACETATE, TBHQ